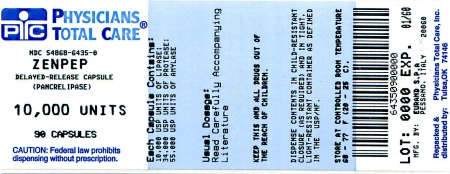 DRUG LABEL: ZENPEP
NDC: 54868-6435 | Form: CAPSULE, DELAYED RELEASE
Manufacturer: Physicians Total Care, Inc.
Category: prescription | Type: HUMAN PRESCRIPTION DRUG LABEL
Date: 20140915

ACTIVE INGREDIENTS: PANCRELIPASE LIPASE 10000 [USP'U]/1 1; PANCRELIPASE PROTEASE 34000 [USP'U]/1 1; PANCRELIPASE AMYLASE 55000 [USP'U]/1 1
INACTIVE INGREDIENTS: CROSCARMELLOSE SODIUM; HYDROGENATED CASTOR OIL; SILICON DIOXIDE; CELLULOSE, MICROCRYSTALLINE; MAGNESIUM STEARATE; TALC; TRIETHYL CITRATE; HYPROMELLOSE PHTHALATE (31% PHTHALATE, 170 CST); CARRAGEENAN; POTASSIUM CHLORIDE; TITANIUM DIOXIDE; HYPROMELLOSES; WATER; FERRIC OXIDE YELLOW

HIGHLIGHTS OF PRESCRIBING INFORMATION

These highlights do not include all the information needed to use ZENPEP safely and effectively. See full prescribing information for ZENPEP.
ZENPEP® (pancrelipase) delayed release capsules
Initial U.S. Approval: 2009

1 INDICATIONS AND USAGE

ZENPEP® is a combination of porcine-derived lipases, proteases, and amylases indicated for the treatment of exocrine pancreatic insufficiency due to cystic fibrosis, or other conditions (1)

2 DOSAGE AND ADMINISTRATION

Dosage
ZENPEP is not interchangeable with any other pancrelipase product.
Infants (up to 12 months)

- Infants may be given 3,000 lipase units (one capsule) per 120 mL of formula or per breast-feeding. (2.1)
- Do not mix ZENPEP capsule contents directly into formula or breast milk prior to administration. (2.2)

Children Older than 12 Months and Younger than 4 Years

- Enzyme dosing should begin with 1,000 lipase units/kg of body weight per meal to a maximum of 2,500 lipase units/kg of body weight per meal (or less than or equal to 10,000 lipase units/kg of body weight per day), or less than 4,000 lipase units/g fat ingested per day. (2.1)

Children 4 Years and Older and Adults

- Enzyme dosing should begin with 500 lipase units/kg of body weight per meal to a maximum of 2,500 lipase units/kg of body weight per meal (or less than or equal to 10,000 lipase units/kg of body weight per day), or less than 4,000 lipase units/g fat ingested per day. (2.1)

Limitations on Dosing

- Dosing should not exceed the recommended maximum dosage set forth by the Cystic Fibrosis Foundation Consensus Conferences Guidelines (2.1)

Administration

- ZENPEP should be swallowed whole. For infants or patients unable to swallow intact capsules, the contents may be sprinkled on soft acidic food, e.g., applesauce. (2.2)

3 DOSAGE FORMS AND STRENGTHS

- Capsules: 3,000 USP units of lipase; 10,000 USP units of protease; 16,000 USP units of amylase. Capsules have a white opaque cap and body, printed with “EURAND 3” (3)
- Capsules: 5,000 USP units of lipase; 17,000 USP units of protease; 27,000 USP units of amylase. Capsules have a white opaque cap and body, printed with “EURAND 5” (3)
- Capsules: 10,000 USP units of lipase; 34,000 USP units of protease; 55,000 USP units of amylase. Capsules have a yellow opaque cap and white opaque body, printed with “EURAND 10” (3)
- Capsules: 15,000 USP units of lipase; 51,000 USP units of protease; 82,000 USP units of amylase. Capsules have a red opaque cap and white opaque body, printed with “EURAND 15” (3)
- Capsules: 20,000 USP units of lipase; 68,000 USP units of protease; 109,000 USP units of amylase. Capsules have a green opaque cap and white opaque body, printed with “EURAND 20”(3)
- Capsules: 25,000 USP units of lipase; 85,000 USP units of protease; 136,000 USP units of amylase. Capsules have a blue opaque cap and white opaque body, printed with “EURAND 25"(3)

4 CONTRAINDICATIONS

None (4)

5 WARNINGS AND PRECAUTIONS

- Fibrosing colonopathy is associated with high-dose use of pancreatic enzyme replacement. Exercise caution when doses of ZENPEP exceed 2,500 lipase units/kg of body weight per meal (or greater than 10,000 lipase units/kg of body weight per day). (5.1)
- To avoid irritation of oral mucosa, do not chew ZENPEP or retain in the mouth. (5.2)
- Exercise caution when prescribing ZENPEP to patients with gout, renal impairment, or hyperuricemia. (5.3)
- There is theoretical risk of viral transmission with all pancreatic enzyme products including ZENPEP. (5.4)
- Exercise caution when administering pancrelipase to a patient with a known allergy to proteins of porcine origin. (5.5)

6 ADVERSE REACTIONS

- The most common adverse events (≥6% of patients treated with ZENPEP) are abdominal pain, flatulence, headache, cough, decreased weight, early satiety, and contusion. (6.1)

To report SUSPECTED ADVERSE REACTIONS, contact Aptalis Pharma at 1-888-936-7371 or FDA at 1-800-FDA-1088 or www.fda.gov/medwatch

8 USE IN SPECIFIC POPULATIONS

Pediatric Patients:

- The safety and effectiveness of ZENPEP were assessed in pediatric patients, ages 1 to 17 years. (8.4)
- The safety and efficacy of pancreatic enzyme products with different formulations of pancrelipase in pediatric patients have been described in the medical literature and through clinical experience. (8.4)

FULL PRESCRIBING INFORMATION

1 INDICATIONS AND USAGE

ZENPEP® (pancrelipase) is indicated for the treatment of exocrine pancreatic insufficiency due to cystic fibrosis or other conditions.

2 DOSAGE AND ADMINISTRATION

2.1 Dosage

ZENPEP is not interchangeable with other pancrelipase products.

ZENPEP is orally administered. Therapy should be initiated at the lowest recommended dose and gradually increased. The dosage of ZENPEP should be individualized based on clinical symptoms, the degree of steatorrhea present, and the fat content of the diet (see Limitations on Dosing below).

Dosage recommendations for pancreatic enzyme replacement therapy were published following the Cystic Fibrosis Foundation Consensus Conferences.^(1, 2, 3) ZENPEP should be administered in a manner consistent with the recommendations of the Conferences provided in the following paragraphs, with one exception. The Conferences recommend doses of 2,000 to 4,000 lipase units in infants up to 12 months. ZENPEP is available in a 3,000 lipase unit capsule. The recommended dose of ZENPEP in infants up to 12 months is 3,000 lipase units. Patients may be dosed on a fat ingestion-based or actual body weight-based dosing scheme.

Infants (up to 12 months)
Infants may be given 3,000 lipase units (one capsule) per 120 mL of formula or breast-feeding. Do not mix ZENPEP capsule contents directly into formula or breast milk prior to administration [see Dosage and Administration (2.2)].

Children Older than 12 Months and Younger than 4 Years
Enzyme dosing should begin with 1,000 lipase units/kg of body weight per meal for children less than age 4 years to a maximum of 2,500 lipase units/kg of body weight per meal (or less than or equal to 10,000 lipase units/kg of body weight per day), or less than 4,000 lipase units/g fat ingested per day.

Children 4 Years and Older and Adults
Enzyme dosing should begin with 500 lipase units/kg of body weight per meal for those older than age 4 years to a maximum of 2,500 lipase units/kg of body weight per meal (or less than or equal to 10,000 lipase units/kg of body weight per day), or less than 4,000 lipase units/g fat ingested per day.

Usually, half of the prescribed ZENPEP dose for an individualized full meal should be given with each snack. The total daily dose should reflect approximately three meals plus two or three snacks per day.

Enzyme doses expressed as lipase units/kg of body weight per meal should be decreased in older patients because they weigh more but tend to ingest less fat per kilogram of body weight.

Limitations on Dosing
Dosing should not exceed the recommended maximum dosage set forth by the Cystic Fibrosis Foundation Consensus Conferences Guidelines.^(1, 2, 3)

If symptoms and signs of steatorrhea persist, the dosage may be increased by a healthcare professional. Patients should be instructed not to increase the dosage on their own. There is great inter-individual variation in response to enzymes; thus, a range of doses is recommended. Changes in dosage may require an adjustment period of several days. If doses are to exceed 2,500 lipase units/kg of body weight per meal, further investigation is warranted.

Doses greater than 2,500 lipase units/kg of body weight per meal (or greater than 10,000 lipase units/kg of body weight per day) should be used with caution and only if they are documented to be effective by 3-day fecal fat measures that indicate a significantly improved coefficient of fat absorption. Doses greater than 6000 lipase units/kg of body weight per meal have been associated with colonic strictures, indicative of fibrosing colonopathy, in children with cystic fibrosis less than 12 years of age [see Warnings and Precautions (5.1)]. Patients currently receiving higher doses than 6,000 lipase units/kg of body weight per meal should be examined and the dosage either immediately decreased or titrated downward to a lower range.

2.2 Administration

ZENPEP should always be taken as prescribed by a healthcare professional.

Infants (up to 12 months)
ZENPEP should be administered to infants immediately prior to each feeding, using a dosage of 3,000 lipase units (one capsule) per 120 mL of formula or per breast-feeding. Contents of the capsule may be administered with a small amount of applesauce, or other acidic food with a pH of 4.5 or less (e.g., commercially available preparations of bananas, or pears). Contents of the capsule may also be administered directly to the mouth. Administration should be followed by breast milk or formula. Contents of the capsule should not be mixed directly into formula or breast milk as this may diminish efficacy. Care should be taken to ensure that ZENPEP is not crushed or chewed or retained in the mouth, to avoid irritation of the oral mucosa.

Children and Adults
ZENPEP should be taken during meals or snacks, with sufficient fluid. ZENPEP capsules and capsule contents should not be crushed or chewed. Capsules should be swallowed whole.

For patients who are unable to swallow intact capsules, the capsules may be carefully opened and the contents sprinkled on small amounts of acidic soft food of pH 4.5 or less (e.g., commercially available preparations of bananas, pears and applesauce).

The ZENPEP -soft food mixture should be swallowed immediately without crushing or chewing, and followed with water or juice to ensure complete ingestion. Care should be taken to ensure that no drug is retained in the mouth.

3 DOSAGE FORMS AND STRENGTHS

The active ingredient in ZENPEP evaluated in clinical trials is lipase. ZENPEP is dosed by lipase units.

ZENPEP is available in 6 color coded capsule strengths.
Other active ingredients include protease and amylase. Each ZENPEP capsule strength contains the specified amounts of lipase, protease, and amylase.

Capsules of all strengths have a blue radial print on the capsule body and are colored as follows:

- 3,000 USP units of lipase; 10,000 USP units of protease; 16,000 USP units of amylase capsules have a white opaque cap and white opaque body, red imprint with “EURAND 3”
- 5,000 USP units of lipase; 17,000 USP units of protease; 27,000 USP units of amylase capsules have a white opaque cap and white opaque body, printed with “EURAND 5”
- 10,000 USP units of lipase; 34,000 USP units of protease; 55,000 USP units of amylase capsules have a yellow opaque cap and white opaque body, printed with “EURAND 10”
- 15,000 USP units of lipase; 51,000 USP units of protease; 82,000 USP units of amylase capsules have a red opaque cap and white opaque body, printed with “EURAND 15”
- 20,000 USP units of lipase; 68,000 USP units of protease; 109,000 USP units of amylase capsules have a green opaque cap and white opaque body, printed with “EURAND 20”
- 25,000 USP units of lipase; 85,000 USP units of protease; 136,000 USP units of amylase capsules have a blue opaque cap and white opaque body, blue imprint with “EURAND 25”

4 CONTRAINDICATIONS

None.

5 WARNINGS AND PRECAUTIONS

5.1 Fibrosing Colonopathy

Fibrosing colonopathy has been reported following treatment with different pancreatic enzyme products. Fibrosing colonopathy is a rare serious adverse reaction initially described in association with high-dose pancreatic enzyme use, usually with use over a prolonged period of time and most commonly reported in pediatric patients with cystic fibrosis. The underlying mechanism of fibrosing colonopathy remains unknown. Doses of pancreatic enzyme products exceeding 6000 lipase units/kg of body weight per meal have been associated with colonic strictures in children less than 12 years of age.^1 Patients with fibrosing colonopathy should be closely monitored because some patients may be at risk of progressing to stricture formation. It is uncertain whether regression of fibrosing colonopathy occurs. It is generally recommended, unless clinically indicated, that enzyme doses should be less than 2,500 lipase units/kg of body weight per meal (or less than 10,000 lipase units/kg of body weight per day) or less than 4,000 lipase units/g fat ingested per day [see Dosage and Administration (2.1)].

Doses greater than 2,500 lipase units/kg of body weight per meal (or greater than 10,000 lipase units/kg of body weight per day) should be used with caution and only if they are documented to be effective by 3-day fecal fat measures that indicate a significantly improved coefficient of fat absorption. Patients receiving higher doses than 6,000 lipase units/kg of body weight per meal should be examined and the dosage either immediately decreased or titrated downward to a lower range.

5.2 Potential for Irritation to Oral Mucosa

Care should be taken to ensure that no drug is retained in the mouth. ZENPEP should not be crushed or chewed or mixed in foods having a pH greater than 4.5. These actions can disrupt the protective enteric coating resulting in early release of enzymes, irritation of oral mucosa, and/or loss or enzyme activity [see Dosage and Administration (2.2) and Patient Counseling Information (17.1)]. For patients who are unable to swallow intact capsules, the capsules may be carefully opened and the contents added to a small amount of acidic soft food with a pH of 4.5 or less, such as applesauce. The ZENPEP-soft food mixture should be swallowed immediately and followed with water or juice to ensure complete ingestion.

5.3 Potential for Risk of Hyperuricemia

Caution should be exercised when prescribing ZENPEP to patients with gout, renal impairment, or hyperuricemia. Porcine-derived pancreatic enzyme products contain purines that may increase blood uric acid levels.

5.4 Potential Viral Exposure from the Product Source

ZENPEP is sourced from pancreatic tissue from swine used for food consumption. Although the risk that ZENPEP will transmit an infectious agent to humans has been reduced by testing for certain viruses during manufacturing and by inactivating certain viruses during manufacturing, there is a theoretical risk for transmission of viral disease, including diseases caused by novel or unidentified viruses. Thus, the presence of porcine viruses that might infect humans cannot be definitely excluded. However, no cases of transmission of an infectious illness associated with the use of porcine pancreatic extracts have been reported.

5.5 Allergic Reactions

Caution should be exercised when administering pancrelipase to a patient with a known allergy to proteins of porcine origin. Rarely, severe allergic reactions including anaphylaxis, asthma, hives, and pruritus, have been reported with other pancreatic enzyme products with different formulations of the same active ingredient (pancrelipase). The risks and benefits of continued ZENPEP treatment in patients with severe allergy should be taken into consideration with the overall clinical needs of the patient.

6 ADVERSE REACTIONS

The most serious adverse reactions reported with different pancreatic enzyme products of the same active ingredient (pancrelipase) include fibrosing colonopathy, hyperuricemia and allergic reactions [see Warnings and Precautions, (5)]

6.1 Clinical Trials Experience

Because clinical trials are conducted under widely varying conditions, adverse reaction rates observed in the clinical trials of a drug cannot be directly compared to the rates in the clinical trials of another drug and may not reflect the rates observed in clinical practice.

The short-term safety of ZENPEP was assessed in two clinical trials conducted in 53 patients, ages 1 to 23 years, with exocrine pancreatic insufficiency (EPI) due to CF. In both studies, ZENPEP was administered in doses of approximately 5,000 lipase units per kilogram per day, for lengths of treatment ranging from 19 to 42 days. The population was nearly evenly distributed in gender, and approximately 96% of patients were Caucasian.

Study 1 was a randomized, double-blind, placebo-controlled, 2-treatment, crossover study of 34 patients, ages 7 to 23 years, with EPI due to CF. In this study, patients were randomized to receive ZENPEP at individually titrated doses (not to exceed 2,500 lipase units per kilogram per meal) or matching placebo for 6 to 7 days of treatment, followed by crossover to the alternate treatment for an additional 6 to 7 days. The mean exposure to ZENPEP during this study, including titration period and open label transition, was 30 days.

The incidence of adverse events (regardless of causality) was similar during double blind ZENPEP treatment (56%) and placebo treatment (50%). The most common adverse events reported during the study were gastrointestinal complaints, which were reported more commonly during placebo treatment (41%) than during ZENPEP treatment (32%), and headache, which was reported more commonly during ZENPEP treatment (15%) than during placebo treatment (0). The type and incidence of adverse events were similar in children (7-11 years), adolescents (12-16 years), and adults (greater than 18 years).

Because clinical trials are conducted under controlled conditions, the observed adverse event rates may not reflect the rates observed in clinical practice.

Table 1 enumerates treatment-emergent adverse events that occurred in at least 2 patients (greater than or equal to 6%) treated with either ZENPEP or placebo in Study 1. Adverse events were classified by Medical Dictionary for Regulatory Activities (MedDRA) terminology.

Table 1: Treatment-Emergent Adverse Events Occurring in at least 2 Patients (greater than or equal to 6%) During Treatment Period and Crossover Treatment Period of the Placebo-Controlled, Crossover Clinical Study of ZENPEP (Study 1)

MedDRA Primary System Organ Class Preferred Term | ZENPEP (N=34) % | Placebo (N=32) %
Gastrointestinal Disorders
Abdominal pain | 6 (18%) | 9 (28%)
Flatulence | 2 (6%) | 3 (9%)
Nervous System Disorders
Headache | 5 (15%) | 0
Injury, Poisoning and Procedural Complications
Contusion | 2 (6%) | 0
Investigations
Weight decreased | 2 (6%) | 2 (6%)
Respiratory, Thoracic and Mediastinal Disorders
Cough | 2 (6%) | 0
General Disorders and Administration Site Conditions
Early Satiety | 2 (6%) | 0

Study 2 was an open-label, uncontrolled study of 19 patients, ages 1 to 6 years, with EPI due to CF. After a 4-14 days screening period on the current PEP, patients in Study 2 received ZENPEP at individually titrated doses ranging between 2,300 and 10,000 lipase units per kg body weight per day, with a mean of approximately 5000 lipase units per kg body weight per day (not to exceed 2,500 lipase units per kilogram per meal) for 14 days. There was no comparator treatment, and adverse events were collected on patient diary entries and at each study visit.

The most commonly reported adverse events were gastrointestinal, including abdominal pain and steatorrhea, and were similar in type and frequency to those reported in the double-blind, placebo-controlled trial (Study 1).

6.2 Postmarketing Experience

Postmarketing data for ZENPEP have been available since 2009. The following adverse reactions have been identified during post-approval use of Zenpep. Because these reactions are reported voluntarily from a population of uncertain size, it is not always possible to reliably estimate their frequency or establish a causal relationship to drug exposure.

The most commonly reported adverse events are gastrointestinal disorders (including abdominal distension, abdominal pain, diarrhea, flatulence, constipation and nausea) and skin disorders (including pruritus, urticaria, and rash).

In patients at risk for abnormal blood glucose levels glycemic control may be affected by administration of pancreatic enzyme replacement therapy. Consideration should be given to additional glucose monitoring in these patients.

Delayed- and immediate-release pancreatic enzyme products with different formulations of the same active ingredient (pancrelipase) have been used for the treatment of patients with exocrine pancreatic insufficiency due to cystic fibrosis and other conditions, such as chronic pancreatitis. The long-term safety profile of these products has been described in the medical literature. The most serious adverse events include fibrosing colonopathy, distal intestinal obstruction syndrome (DIOS), recurrence of pre-existing carcinoma, and severe allergic reactions including anaphylaxis, asthma, hives, and pruritus.

In general, pancreatic enzyme products have a well defined and favorable risk-benefit profile in exocrine pancreatic insufficiency.

7 DRUG INTERACTIONS

No drug interactions have been identified. No formal interaction studies have been conducted.

8 USE IN SPECIFIC POPULATIONS

8.1 Pregnancy

Teratogenic effects
Pregnancy Category C: Animal reproduction studies have not been conducted with pancrelipase. It is also not known whether pancrelipase can cause fetal harm when administered to a pregnant woman or can affect reproduction capacity. ZENPEP should be given to a pregnant woman only if clearly needed. The risk and benefit of pancrelipase should be considered in the context of the need to provide adequate nutritional support to a pregnant woman with exocrine pancreatic insufficiency. Adequate caloric intake during pregnancy is important for normal maternal weight gain and fetal growth. Reduced maternal weight gain and malnutrition can be associated with adverse pregnancy outcomes.

8.3 Nursing Mothers

It is not known whether this drug is excreted in human milk. Because many drugs are excreted in human milk, caution should be exercised when ZENPEP is administered to a nursing woman. The risk and benefit of pancrelipase should be considered in the context of the need to provide adequate nutritional support to a nursing mother with exocrine pancreatic insufficiency.

8.4 Pediatric Use

The short-term safety and effectiveness of ZENPEP were assessed in 2 clinical studies in pediatric patients, ages 1 to 17 years, with EPI due to CF.

Study 1 was a randomized, double-blind, placebo-controlled, crossover study in 34 patients 26 of whom were children, including 8 children aged 7 to 11 years, and 18 adolescents aged 12 to 17 patients. The safety and efficacy in pediatric patients in this study were similar to adult patients [see Adverse Reactions (6.1) and Clinical Studies (14)].

Study 2 was an open-label, single arm study in 19 patients, ages 1 to 6 years, with EPI due to CF. When patient regimen was switched from their usual PEP regimen to ZENPEP at similar doses, patients showed similar control of their clinical symptoms.

The safety and efficacy of pancreatic enzyme products with different formulations of pancrelipase consisting of the same active ingredient (lipases, proteases, and amylases) for treatment of children with exocrine pancreatic insufficiency due to cystic fibrosis has been described in the medical literature and through clinical experience.

Dosing of pediatric patients should be in accordance with recommended guidance from the Cystic Fibrosis Foundation Consensus Conferences [see Dosage and Administration (2.1)]. Doses of other pancreatic enzyme products exceeding 6,000 lipase units/kg of body weight per meal have been associated with fibrosing colonopathy and colonic strictures in children less than 12 years of age [see Warnings and Precautions (5.1)].

8.5 Geriatric Use

Clinical studies of ZENPEP did not include sufficient numbers of subjects aged 65 and over to determine whether they respond differently from younger subjects. Other reported clinical experience has not identified differences in responses between the elderly and younger patients.

10 OVERDOSAGE

In Study 1, a 10 year-old patient was administered a dose of 10,856 lipase units per kg body weight of ZENPEP for a period of one day. The patient did not experience any adverse events as a result of the dose increase, nor did this patient experience any adverse events during a 44-day follow-up period. No abnormalities from analyses of safety labs (chemistry, hematology, urinalysis or uric acid) were noted.

Chronic high doses of pancreatic enzyme products have been associated with fibrosing colonopathy and colonic strictures [see Dosage and Administration (2.1) and Warnings and Precautions (5.1)]. High doses of pancreatic enzyme products have been associated with hyperuricosuria and hyperuricemia, and should be used with caution in patients with a history of hyperuricemia, gout, or renal impairment [see Warnings and Precautions (5.3)].

11 DESCRIPTION

ZENPEP is a pancreatic enzyme preparation consisting of pancrelipase, an extract derived from porcine pancreatic glands. Pancrelipase contains multiple enzyme classes, including porcine derived lipases, proteases, and amylases.

Pancrelipase is a cream-colored powder. It is miscible in water and practically insoluble or insoluble in alcohol and ether.

Each capsule for oral administration contains enteric-coated beads (1.8-1.9mm for 3,000 and 5,000 USP units of lipase, 2.2-2.5mm for 10,000, 15,000, 20,000 and 25,000 USP units of lipase).

The active ingredient evaluated in clinical trials is lipase. ZENPEP is dosed by lipase units. Other active ingredients include protease and amylase.

Inactive ingredients in ZENPEP include colloidal silicon dioxide, croscarmellose sodium, hydrogenated castor oil, hypromellose phthalate, magnesium stearate, microcrystalline cellulose, talc, and triethyl citrate and are contained in hypromellose capsules. The imprinting red ink on the 3,000 capsules strength contains, antifoam DC 1510, industrial methylated spirit, iron oxide red C.I. 77491-E172, n-butyl alcohol, shellac and soya lecithin.

3,000 USP units of lipase; 10,000 USP units of protease; 16,000 USP units of amylase. Capsules have a white opaque cap and a white opaque body with imprint “EURAND 3”. The shells contain carnauba wax or talc, carrageenan, hypromellose, potassium chloride, titanium oxide, and water.

The imprinting blue ink on the capsules strengths 5,000, 10,000, 15,000, 20,000 and 25,000 contains dehydrated alcohol, FD&C Blue #2 aluminum lake C.I. 73015-E132, isopropyl alcohol, n-butyl alcohol, propylene glycol, shellac and strong ammonia solution.

5,000 USP units of lipase; 17,000 USP units of protease; 27,000 USP units of amylase. Capsules have a white opaque cap and a white opaque body with imprint “EURAND 5”. The shells contain carnauba wax or talc, carrageenan, hypromellose, potassium chloride, titanium oxide, and water.

10,000 USP units of lipase; 34,000 USP units of protease; 55,000 USP units of amylase. Capsules have a yellow opaque cap and a white opaque body with imprint “EURAND 10”. The shells contain carnauba wax or talc, carrageenan, hypromellose, potassium chloride, titanium oxide, water and yellow ferric oxide.

15,000 USP units of lipase; 51,000 USP units of protease; 82,000 USP units of amylase. Capsules have a red opaque cap and a white opaque body with imprint “EURAND 15”. The shells contain carnauba wax or talc, carrageenan, hypromellose, potassium chloride, red ferric oxide, titanium oxide, and water.

20,000 USP units of lipase; 68,000 USP units of protease; 109,000 USP units of amylase. Capsules have a green opaque cap and a white opaque body with imprint “EURAND 20”. The shells contain carnauba wax or talc, carrageenan, FD&C Blue #2, hypromellose, potassium chloride, titanium oxide, water, and yellow ferric oxide.

25,000 USP units of lipase; 85,000 USP units of protease; 136,000 USP units of amylase. Capsules have a blue opaque cap and a white opaque body with imprint “EURAND 25”. The shells contain carnauba wax or talc, carrageenan, FD&C Blue #2, hypromellose, potassium chloride, titanium oxide, and water.

12 CLINICAL PHARMACOLOGY

12.1 Mechanism of Action

The pancreatic enzymes in ZENPEP catalyze the hydrolysis of fats to monoglycerides, glycerol, and free fatty acids, protein into peptides and amino acids, and starch into dextrins and short chain sugars such as maltose and maltriose in the duodenum and proximal small intestine, thereby acting like digestive enzymes physiologically secreted by the pancreas.

12.3 Pharmacokinetics

The pancreatic enzymes in ZENPEP are enteric-coated to minimize destruction or inactivation in gastric acid. ZENPEP is designed to release most of the enzymes in vivo at pH greater than 5.5. Pancreatic enzymes are not absorbed from the gastrointestinal tract in any appreciable amount.

13 NONCLINICAL TOXICOLOGY

13.1 Carcinogenesis, Mutagenesis, Impairment of Fertility

Carcinogenicity, genetic toxicology, and animal fertility studies have not been performed.

14 CLINICAL STUDIES

The short-term safety and efficacy of ZENPEP were evaluated in 2 studies conducted in 53 patients, ages 1 to 23 years, with exocrine pancreatic insufficiency (EPI) associated with cystic fibrosis (CF).

Study 1, was a randomized, double-blind, placebo-controlled, crossover study of 34 patients, ages 7 to 23 years, with EPI due to CF. The final analysis population was limited to 32 patients, who completed both double-blind treatment periods, and were included in the efficacy analysis population. Patients were randomized to receive ZENPEP or matching placebo for 6 to 7 days of treatment, followed by crossover to the alternate treatment for an additional 6 to 7 days. The mean dose during the controlled treatment periods ranged from a mean dose of 3,900 lipase units per kilogram per day to 5,700 lipase units per kilogram per day. All patients consumed a high-fat diet (greater than or equal to 100 grams of fat per day) during the treatment period.

The primary efficacy endpoint was the mean difference in the coefficient of fat absorption (CFA) between ZENPEP and placebo treatment. The CFA was determined by a 72-hour stool collection during both treatments, when both fat excretion and fat ingestion were measured. Each patient’s CFA during placebo treatment was used as their no-treatment CFA value.

Mean CFA was 88% with ZENPEP treatment compared to 63% with placebo treatment. The mean difference in CFA was 26 percentage points in favor of ZENPEP treatment with 95% Confidence Interval of (19, 32) and p≤0.001.

Subgroup analyses of the CFA results showed that mean change in CFA was greater in patients with lower no-treatment (placebo) CFA values than in patients with higher no-treatment (placebo) CFA values. There were similar responses to ZENPEP by age and gender.

Study 2, was an open-label, uncontrolled study of 19 patients, ages 1 to 6 years (mean age 4 years), with EPI due to CF. Approximately half of the patients were ages 1 to 3 years. Study 2 compared a measurement of fat malabsorption, spot fecal fat testing, before (while receiving therapy with another commercial PEP) and after oral administration of Zenpep capsules with each meal or snack.

All patients in Study 2 were transitioned to ZENPEP from their usual PEP treatment. After a 4-14 days screening period on the current PEP, patients in Study 2 received ZENPEP at individually titrated doses ranging between 2,300 and 10,000 lipase units per kg body weight per day, with a mean of approximately 5000 lipase units per kg body weight per day (not to exceed 2,500 lipase units per kilogram per meal) for 14 days. There was no wash-out period. Overall, patients showed similar control of fat malabsorption by spot fecal fat testing when switched to ZENPEP treatment at similar doses.

15 REFERENCES

1. Borowitz DS, Grand RJ, Durie PR, et al. Use of pancreatic enzyme supplements for patients with cystic fibrosis in the context of fibrosing colonopathy. Journal of Pediatrics. 1995; 127: 681-684.
2. Borowitz DS, Baker RD, Stallings V. Consensus report on nutrition for pediatric patients with cystic fibrosis. Journal of Pediatric Gastroenterology Nutrition. 2002 Sep; 35: 246-259.
3. Stallings VA, Start LJ, Robinson KA, et al. Evidence-based practice recommendations for nutrition-related management of children and adults with cystic fibrosis and pancreatic insufficiency: results of a systematic review. Journal of the American Dietetic Association. 2008; 108: 832-839.
4. Smyth RL, Ashby D, O’Hea U, et al. Fibrosing colonopathy in cystic fibrosis: results of a case-control study.9 Lancet. 1995; 346: 1247-1251.
5. FitzSimmons SC, Burkhart GA, Borowitz DS, et al. High-dose pancreatic-enzyme supplements and fibrosing colonopathy in children with cystic fibrosis. New England Journal of Medicine. 1997; 336: 1283-1289

16 HOW SUPPLIED/STORAGE AND HANDLING

ZENPEP® (pancrelipase) Delayed-Release Capsules
3,000 USP units of lipase; 10,000 USP units of protease; 16,000 units of amylase.
Each ZENPEP capsule is available as a two piece hypromellose capsule with white opaque cap and white body with a red radial print and printed with “EURAND 3”, that contains 1.8-1.9mm enteric-coated beads. Capsules are supplied in bottles of:

ZENPEP® (pancrelipase) Delayed-Release Capsules

5,000 USP units of lipase; 17,000 USP units of protease; 27,000 units of amylase.

Each ZENPEP capsule is available as a two piece hypromellose capsule with white opaque cap and white body with a blue radial print and printed with “EURAND 5”, that contains 1.8-1.9mm enteric-coated beads. Capsules are supplied in bottles of:

ZENPEP® (pancrelipase) Delayed-Release Capsules
10,000 USP units of lipase; 34,000 units of protease; 55,000 units of amylase.

Each ZENPEP capsule is available as a two piece hypromellose capsule with yellow opaque cap and white body with a blue radial print and printed with “EURAND 10”, that contains 2.2-2.5mm enteric-coated beads. Capsules are supplied in bottles of:

- 90 capsules (NDC 54868-6435-0)

ZENPEP® (pancrelipase) Delayed-Release Capsules
15,000 USP units of lipase; 51,000 units of protease; 82,000 units of amylase.

Each ZENPEP capsule is available as a two piece hypromellose capsule with red opaque cap and white body with a blue radial print and printed with “EURAND 15”, that contains 2.2-2.5mm enteric-coated beads. Capsules are supplied in bottles of:

ZENPEP® (pancrelipase) Delayed-Release Capsules
20,000 USP units of lipase; 68,000 units of protease; 109,000 units of amylase.

Each ZENPEP capsule is available as a two piece hypromellose capsule with green opaque cap and white body with a blue radial print and printed with “EURAND 20”, that contains 2.2-2.5mm enteric-coated beads. Capsules are supplied in bottles of:

ZENPEP® (pancrelipase) Delayed-Release Capsules
25,000 USP units of lipase; 85,000 units of protease; 136,000 units of amylase.

Each ZENPEP capsule is available as a two piece hypromellose capsule with blue opaque cap and white body with a blue radial print and printed with “EURAND 25”, that contains 2.2-2.5mm enteric-coated beads. Capsules are supplied in bottles of:

Storage and Handling:
Original Glass container:

Avoid excessive heat. Store at room temperature (68-77°F; 20-25°C), brief excursions permitted to 15-40°C (59-104°F). Protect from moisture. AFTER OPENING, KEEP BOTTLE TIGHTLY CLOSED between uses to PROTECT FROM MOISTURE.

Repackaged HDPE container:

Avoid excessive heat. Store up to 30°C (86°F) for up to 6 months. Brief excursions permitted to 15-40°C (59-104°F) for up to 30 days. Protect from moisture. AFTER OPENING, KEEP BOTTLE TIGHTLY CLOSED between uses to PROTECT FROM MOISTURE.

Dispense in tight container (USP).
Keep out of reach of children.

DO NOT CRUSH ZENPEP delayed-release capsules.

17 PATIENT COUNSELING INFORMATION

See FDA-approved patient labeling (Medication Guide)

17.1 Dosing and Administration

- Instruct patients and caregivers that ZENPEP should only be taken as directed by their healthcare professional. Patients should be advised that the total daily dose should not exceed 10,000 lipase units/kg body weight per day unless clinically indicated. This needs to be especially emphasized for patients eating multiple snacks and meals per day. Patients should be informed that if a dose is missed, the next dose should be taken with the next meal or snack as directed. Doses should not be doubled.[see Dosage and Administration (2)].
- Instruct patients and caregivers that ZENPEP should always be taken with food. Patients should be advised that ZENPEP delayed-release capsules must not be crushed or chewed as doing so could cause early release of enzymes and/or loss of enzymatic activity. Patients should swallow the intact capsules with adequate amounts of liquid at mealtimes. If necessary, the capsules contents can also be sprinkled on soft acidic foods. [see Dosage and Administration (2)].
- Instruct patients to notify their healthcare professional if they are pregnant or are thinking of becoming pregnant during treatment with ZENPEP. [see Use in Specific Populations (8.1).]
- Instruct patients and caregivers to notify the healthcare professional if the patient has a history of abnormal glucose levels before initiating treatment with ZENPEP. [see Postmarketing Experience (6.2)].

17.2 Fibrosing Colonopathy

Advise patients and caregivers to follow dosing instructions carefully, as doses of pancreatic enzyme products exceeding 6,000 lipase units/kg of body weight per meal (10,000 lipase units/kg body weight/day) have been associated with colonic strictures in children below the age of 12 years. [see Dosage and Administration (2)].

17.3 Allergic Reactions

Advise patients and caregivers to contact their healthcare professional immediately if allergic reactions to ZENPEP develop. [see Warnings and Precautions (5.5)].

17.4 Pregnancy and Breast Feeding

- Instruct patients to notify their healthcare professional if they are pregnant or thinking of becoming pregnant during treatment with ZENPEP [see Use in Specific Populations (8.1)].
- Instruct patients to notify their healthcare professional if they are breast feeding or thinking of breast feeding during treatment with ZENPEP [see Use in Specific Populations (8.3)].

ZENPEP® is subject of US Patent No. 7,658,918.

Manufactured by:

Aptalis Pharma S.r.l.
Via Martin Luther King, 13
20060, Pessano con Bornago
Milan, Italy

Marketed by:

Aptalis Pharma US, Inc.

100 Somerset Corporate Boulevard
Bridgewater, NJ 08807

USA

For further information, please call Aptalis Pharma toll-free at 1-888-936-7371.

©2013 Aptalis Pharma US, Inc.
PKG-1028
3/18 rev. 6

Distributed by:

Physicians Total Care, Inc.

Tulsa, OK 74146

MEDICATION GUIDE

ZENPEP® (ZEN-pep)
(pancrelipase)
Delayed-Release Capsules

Read this Medication Guide before you start taking ZENPEP and each time you get a refill. There may be new information. This information does not take the place of talking to your doctor about your medical condition or treatment.

What is the most important information I should know about ZENPEP?

- ZENPEP may increase your chance of having a rare bowel disorder called fibrosing colonopathy. This condition is serious and may require surgery. The risk of having this condition may be reduced by following the dosing instructions that your doctor gave you. Call your doctor right away if you have any unusual or severe:
- Stomach area (abdominal) pain
- Bloating
- Trouble passing stool (having bowel movements)
- Nausea, vomiting, or diarrhea

Take ZENPEP exactly as prescribed. Do not take more or less ZENPEP than directed by your doctor.

What is ZENPEP?
ZENPEP is a prescription medicine for people who cannot digest food normally because their pancreas does not make enough enzymes. ZENPEP may help your body use fats, proteins and sugars from food.
ZENPEP contains a mixture of digestive enzymes including lipases, proteases, and amylases from pig pancreas.
ZENPEP is safe and effective in children.

What should I tell my doctor before taking ZENPEP?

Before taking ZENPEP, tell your doctor about all your medical conditions, including if you

- are allergic to pork (pig) products.
- have a history of blockage of your intestines, or scarring or thickening of your bowel wall (fibrosing colonopathy)
- have gout, kidney disease, or high blood uric acid (hyperuricemia)
- have trouble swallowing capsules
- have any other medical condition
- are pregnant or plan to become pregnant. It is not known if ZENPEP will harm your unborn baby. Talk to your doctor if you are pregnant or plan to become pregnant.
- are breast-feeding or plan to breast-feed. It is not known if ZENPEP passes into your breast milk. You and your doctor should decide if you will take ZENPEP or breastfeed.

Tell your doctor about all the medicines you take, including prescription and nonprescription medicines, vitamins, and dietary or herbal supplements. Know the medicines you take. Keep a list of them and show it to your doctor and pharmacist when you get a new medicine.

How should I take ZENPEP? Take ZENPEP exactly as your doctor tells you.

- Do not take more capsules in a day than the number your doctor tells you (total daily dose).
- Always take ZENPEP with a meal or snack. If you eat a lot of meals or snacks in a day, be careful not to go over your total daily dose.
- Do not crush or chew the ZENPEP capsules or its contents, and do not hold the capsule or contents in your mouth. Crushing, chewing or holding the ZENPEP Capsules in your mouth may cause irritation in your mouth or change the way ZENPEP works in your body

Giving ZENPEP to children and adults

- Swallow ZENPEP capsules whole and take them with enough liquid to swallow them right away.
- If you have trouble swallowing capsules, open the capsules and sprinkle the beads on a small amount of acidic food such as applesauce, pureed bananas or pears. Ask your doctor about other foods you can mix with ZENPEP.
- If you sprinkle ZENPEP on food, swallow it right after you mix it. Do not store ZENPEP that is mixed with food.
- Swallow the ZENPEP and food mixture right away followed with water or juice. Make sure the medicine is swallowed completely.
- If you forget to take ZENPEP, call your doctor or wait until your next meal and take your usual number of capsules. Do not make up for missed doses. Take your next dose at the usual time.

Giving ZENPEP to infants (children up to 12 months):

1. Give ZENPEP right before each feeding of formula or breast milk.
2. Do not mix ZENPEP capsule contents directly into formula or breast milk.
3. Open the capsule and sprinkle the contents on a small amount of applesauce, pureed bananas or pears. These foods should be the kind found in baby food jars that you buy at the store, or other food recommended by your doctor. You may also sprinkle the contents directly into your child’s mouth.
4. If you sprinkle the ZENPEP on food, give the ZENPEP and food mixture to your child right away.
5. Give your child enough liquid to completely swallow the ZENPEP contents or the ZENPEP and food mixture.
6. Look in your child’s mouth to make sure that all of the medicine has been swallowed.

What are possible side effects of ZENPEP?

ZENPEP may cause serious side effects, including:

See “What is the most important information I should know about ZENPEP?”

- Worsening of swollen, painful joints (gout) caused by an increase in your blood uric acid levels
- Allergic reactions including trouble with breathing, skin rashes, or swollen lips.

Call your doctor right away if you have any of these symptoms.
The most common side effects of ZENPEP include

- Pain in your belly
- Gas
- Headache

Other Possible Side Effects
ZENPEP and other pancreatic enzyme products are made from the pancreas of pigs, the same pigs people eat as pork. These pigs may carry viruses. Although it has never been reported, it may be possible for a person to get a viral infection from taking pancreatic enzyme products that come from pigs.
Tell your doctor if you have any side effect that bothers you or does not go away.
These are not all the possible side effects of ZENPEP. For more information, ask your doctor or pharmacist.

Call your doctor for medical advice about side effects. You may report side effects to FDA at 1-800-FDA-1088.

You may also report side effects to Aptalis Pharma at 1-888-936-7371.

How do I store ZENPEP?

- Store ZENPEP at room temperature (68° to 77°F; 20°C to 25°C). Avoid heat.
- After opening the bottle, keep it closed tightly between doses
- DO NOT eat or throw away the packet (desiccant) in your medicine bottle. This packet will protect your medicine from moisture.
- Store ZENPEP in a dry place.

Keep ZENPEP and all medicines out of the reach of children.

General information about ZENPEP
Medicines are sometimes prescribed for purposes other than those listed in a Medication Guide. Do not use ZENPEP for a condition for which it was not prescribed. Do not give ZENPEP to other people, even if they have the same symptoms you have. It may harm them.
This Medication Guide summarizes the most important information about ZENPEP. If you would like more information, talk with your doctor. You can ask your pharmacist or doctor for information about ZENPEP that is written for health professionals. For more information, go to www.ZENPEP.com or call 1-888-ZENPEP1 (1-888-936-7371).

What are the ingredients in ZENPEP?
Active ingredient: lipase, protease, amylase
Inactive ingredients: colloidal silicon dioxide, croscarmellose sodium, hydrogenated castor oil, hypromellose phthalate, magnesium stearate, microcrystalline cellulose, talc, and triethyl citrate in hypromellose capsules.

The red radial imprinting on the 3,000 capsule strength contains, antifoam DC 1510, industrial methylated spirit, iron oxide red C.I. 77491-E172, n-butyl alcohol, shellac and soya lecithin.

The blue radial imprinting on the 5,000, 10,000, 15,000, 20,000 and 25,000 capsule strengths contains dehydrated alcohol, FD&C Blue #2 aluminum lake C.I. 73015-E132, isopropyl alcohol, n-butyl alcohol, propylene glycol, shellac and strong ammonia solution.

This Medication Guide has been approved by the U.S. Food and Drug Administration.

Manufactured by:

Aptalis Pharma S.r.l.
Via Martin Luther King, 13
20060, Pessano con Bornago
Milan, Italy

Marketed by:
Aptalis Pharma US, Inc.
100 Somerset Corporate Boulevard
Bridgewater, NJ 08807
USA

©2013 Aptalis Pharma US, Inc.

Issued April 2013
PKG-1046
3/18 rev. 5

Package Label - Principal Display Panel – 10000 unit capsule